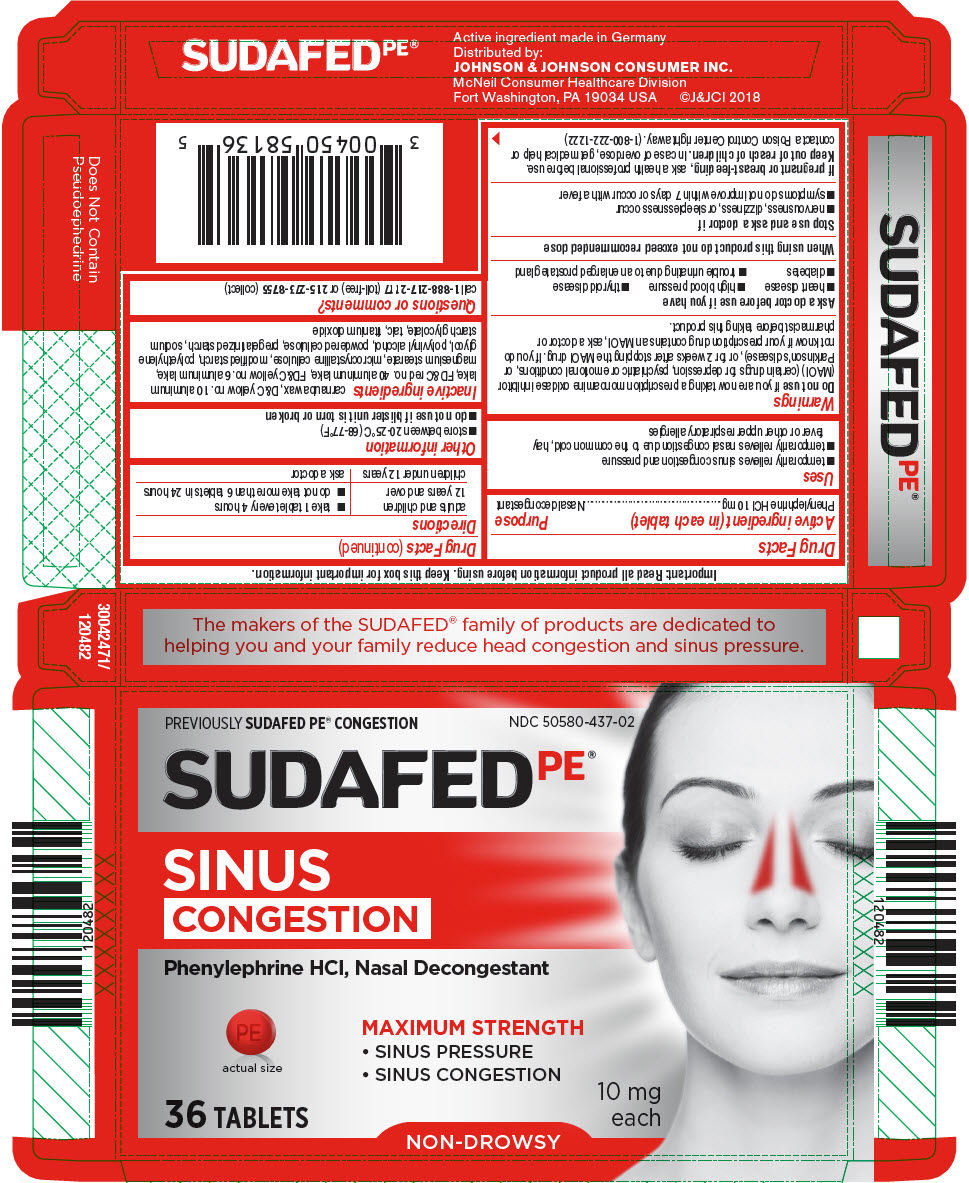 DRUG LABEL: Sudafed PE Sinus Congestion
NDC: 50580-437 | Form: TABLET, FILM COATED
Manufacturer: Kenvue Brands LLC
Category: otc | Type: HUMAN OTC DRUG LABEL
Date: 20241108

ACTIVE INGREDIENTS: PHENYLEPHRINE HYDROCHLORIDE 10 mg/1 1
INACTIVE INGREDIENTS: CARNAUBA WAX; D&C YELLOW NO. 10 ALUMINUM LAKE; ALUMINUM OXIDE; FD&C RED NO. 40; FD&C YELLOW NO. 6; MAGNESIUM STEARATE; MICROCRYSTALLINE CELLULOSE; POLYETHYLENE GLYCOL, UNSPECIFIED; POLYVINYL ALCOHOL, UNSPECIFIED; POWDERED CELLULOSE; SODIUM STARCH GLYCOLATE TYPE A; TALC; TITANIUM DIOXIDE

Sudafed PE Sinus Congestion

Drug Facts

Active ingredient (in each tablet)

Phenylephrine HCl 10 mg

Purpose

Nasal decongestant

Uses

- temporarily relieves sinus congestion and pressure
- temporarily relieves nasal congestion due to the common cold, hay fever or other upper respiratory allergies

Warnings

Do not use if you are now taking a prescription monoamine oxidase inhibitor (MAOI) (certain drugs for depression, psychiatric or emotional conditions, or Parkinson's disease), or for 2 weeks after stopping the MAOI drug. If you do not know if your prescription drug contains an MAOI, ask a doctor or pharmacist before taking this product.

Ask a doctor before use if you have

- heart disease
- high blood pressure
- thyroid disease
- diabetes
- trouble urinating due to an enlarged prostate gland

When using this product do not exceed recommended dose

Stop use and ask a doctor if

- nervousness, dizziness, or sleeplessness occur
- symptoms do not improve within 7 days or occur with a fever

PREGNANCY OR BREAST FEEDING

If pregnant or breast-feeding, ask a health professional before use.

Keep out of reach of children. In case of overdose, get medical help or contact a Poison Control Center right away. (1-800-222-1222)

Directions

adults and children 12 years and over | - take 1 tablet every 4 hours - do not take more than 6 tablets in 24 hours
children under 12 years | ask a doctor

Other information

- store between 20-25°C (68-77°F)
- do not use if blister unit is torn or broken

Inactive ingredients

carnauba wax, D&C yellow no. 10 aluminum lake, FD&C red no. 40 aluminum lake, FD&C yellow no. 6 aluminum lake, magnesium stearate, microcrystalline cellulose, modified starch, polyethylene glycol, polyvinyl alcohol, powdered cellulose, pregelatinized starch, sodium starch glycolate, talc, titanium dioxide

Questions or comments?

call 1-888-217-2117 (toll-free) or 215-273-8755 (collect)

PRINCIPAL DISPLAY PANEL

PREVIOUSLY SUDAFED PE® CONGESTION
NDC 50580-437-02

SUDAFEDPE®

SINUS
CONGESTION

Phenylephrine HCl, Nasal Decongestant

actual size

MAXIMUM STRENGTH

- SINUS PRESSURE
- SINUS CONGESTION

36 TABLETS

NON-DROWSY

10 mg
each